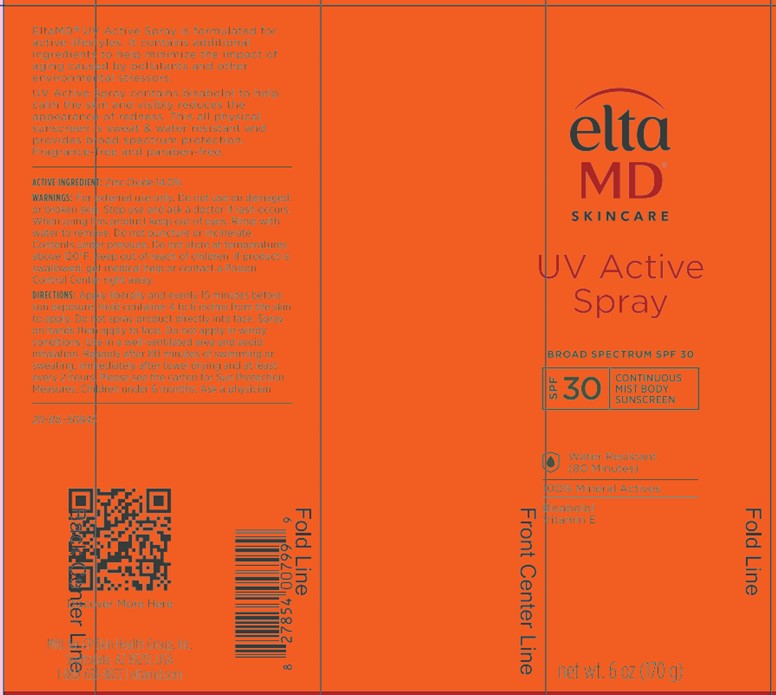 DRUG LABEL: Elta MD
NDC: 72043-4341 | Form: SPRAY
Manufacturer: CP Skin Health Group, Inc.
Category: otc | Type: HUMAN OTC DRUG LABEL
Date: 20231214

ACTIVE INGREDIENTS: ZINC OXIDE 14 g/100 g
INACTIVE INGREDIENTS: WATER

Elta MD UV Active Spray

Warnings

For external use only

Do not use

on damaged or broken skin

When using this product

keep out of eyes. Rinse with water to remove.

Stop use and ask a physician

if rash occurs

Inactive Ingredients

Caprylic/Capric Triglyceride, Helianthys Annuus (Sunflower) Seed Wax, Cerearyl Nonanoate, Theobroma Cacao Cocoa) Seed Butter, Butyloctyl Salicylate, Lauryl Laurate, Polyhydroxystearic Acid, Euphorbia Cerifera (Candelilla) Was, Capryloyl Glycerin/Sebacic Acid Copolymer, Mica, Behenyl Behenate, Butyrospermum Parkii (Shea) Butter, Oryzanol, Ethyl Ferulate, Isostearic Acid, Lecithin, Polyglyceryl-3 Plyricinoleate, Bisabolol, Tocopherol, Silica

Uses

helps prevent sunburn
if used as directed with other sun protection measures (seeDirections), decreases the risk of UV damage and early skin aging caused by the sun

KEEP OUT OF REACH OF CHILDREN

If product is swallowed, get medical help or contact a Poison Control Center right away.

PURPOSE

Sunscreen

DOSAGE AND ADMINISTRATION

Apply liberally 15 minutes before sun exposure
Reapply: after 80 minutes of swimming or sweating: immediately after towel drying: at lear every 2 hours
Sun Protection Measures

Spending time in the sun can increase your riske of skin cancer and early skin aging.
To decrease this risk regularly use a sunscreen with a broad spectrum SPF 15 of 15 or higher and other sun protection measures including:

Limit time in the sun, especially from 10 a.m. - 2 p.m.
Wear long-sleeve shirts, pants, hats, and sunglasses
Children under 6 months:Ask a physician